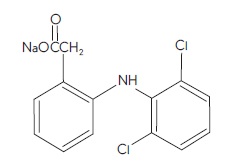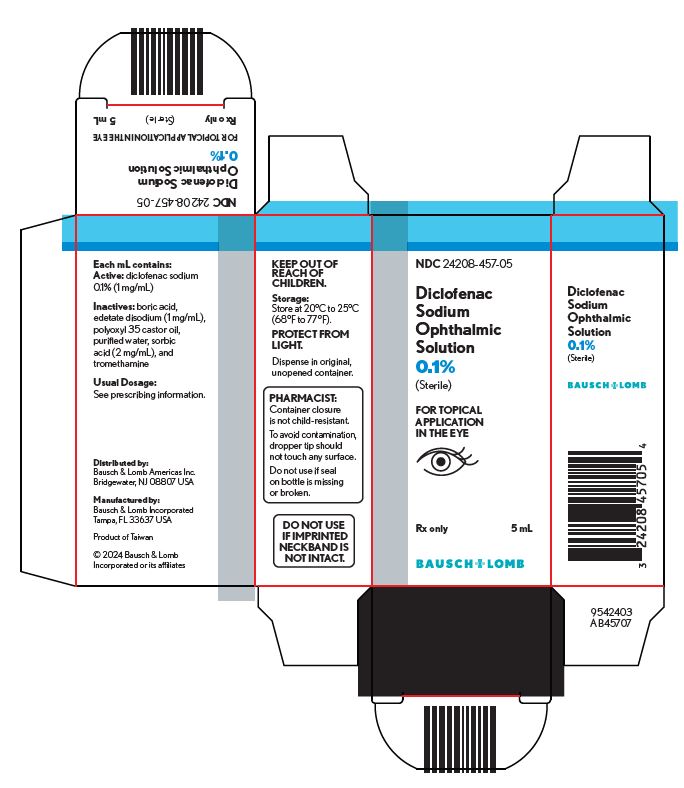 DRUG LABEL: Diclofenac Sodium
NDC: 24208-457 | Form: SOLUTION/ DROPS
Manufacturer: Bausch & Lomb Incorporated
Category: prescription | Type: HUMAN PRESCRIPTION DRUG LABEL
Date: 20260121

ACTIVE INGREDIENTS: DICLOFENAC SODIUM 1 mg/1 mL
INACTIVE INGREDIENTS: BORIC ACID; EDETATE DISODIUM 1 mg/1 mL; POLYOXYL 35 CASTOR OIL; WATER; SORBIC ACID 2 mg/1 mL; TROMETHAMINE

Diclofenac Sodium Ophthalmic
Solution, 0.1%
(Sterile)
Rx only

DESCRIPTION

Diclofenac sodium ophthalmic solution, 0.1% is a sterile, topical, nonsteroidal, anti-inflammatory product for ophthalmic use. Diclofenac sodium is designated chemically as 2-[(2,6-dichlorophenyl)amino] benzeneacetic acid, monosodium salt, with an empirical formula of C14H10Cl2NO2Na. The structural formula of diclofenac sodium is:

Diclofenac sodium ophthalmic solution is available as a sterile solution, which contains diclofenac sodium 0.1% (1 mg/mL).

Inactive Ingredients:boric acid, edetate disodium (1 mg/mL), polyoxyl 35 castor oil, purified water, sorbic acid (2 mg/mL), and tromethamine.

Diclofenac sodium is a white to off-white, hygroscopic crystalline powder. It is freely soluble in methanol, sparingly soluble in water, very slightly soluble in acetonitrile, and insoluble in chloroform and in 0.1N hydrochloric acid. Its molecular weight is 318.14. Diclofenac sodium ophthalmic solution, 0.1% is an iso osmotic solution with an osmolality of about 300 mOsmol/1000 g, buffered at approximately pH 7.2. Diclofenac sodium ophthalmic solution has a faint characteristic odor of castor oil.

CLINICAL PHARMACOLOGY

Pharmacodynamics

Diclofenac sodium is one of a series of phenylacetic acids that has demonstrated anti-inflammatory and analgesic properties in pharmacological studies. It is thought to inhibit the enzyme cyclooxygenase, which is essential in the biosynthesis of prostaglandins.

Animal Studies

Prostaglandins have been shown in many animal models to be mediators of certain kinds of intraocular inflammation. In studies performed in animal eyes, prostaglandins have been shown to produce disruption of the blood-aqueous humor barrier, vasodilation, increased vascular permeability, leukocytosis, and increased intraocular pressure.

Pharmacokinetics

Results from a bioavailability study established that plasma levels of diclofenac following ocular instillation of two drops of diclofenac sodium ophthalmic solution to each eye were below the limit of quantification (10 ng/mL) over a 4-hour period. This study suggests that limited, if any, systemic absorption occurs with diclofenac sodium ophthalmic solution.

Clinical Trials

Postoperative Anti-Inflammatory Effects

In two double-masked, controlled, efficacy studies of postoperative inflammation, a total of 206 cataract patients were treated with diclofenac sodium ophthalmic solution and 103 patients were treated with vehicle placebo. Diclofenac sodium ophthalmic solution was favored over vehicle placebo over a 2-week period for the clinical assessments of inflammation as measured by anterior chamber cells and flare.

In double-masked, controlled studies of corneal refractive surgery (radial keratotomy (RK) and laser photorefractive keratectomy (PRK)) patients were treated with diclofenac sodium ophthalmic solution and/or vehicle placebo. The efficacy of diclofenac sodium ophthalmic solution given before and shortly after surgery was favored over vehicle placebo during the 6-hour period following surgery for the clinical assessments of pain and photophobia. Patients were permitted to use a hydrogel soft contact lens with diclofenac sodium ophthalmic solution for up to three days after PRK.

INDICATIONS AND USAGE

Diclofenac sodium ophthalmic solution is indicated for the treatment of postoperative inflammation in patients who have undergone cataract extraction and for the temporary relief of pain and photophobia in patients undergoing corneal refractive surgery.

CONTRAINDICATIONS

Diclofenac sodium ophthalmic solution is contraindicated in patients who are hypersensitive to any component of the medication.

WARNINGS

The refractive stability of patients undergoing corneal refractive procedures and treated with diclofenac sodium has not been established. Patients should be monitored for a year following use in this setting. With some nonsteroidal anti-inflammatory drugs, there exists the potential for increased bleeding time due to interference with thrombocyte aggregation. There have been reports that ocularly applied nonsteroidal anti-inflammatory drugs may cause increased bleeding of ocular tissues (including hyphemas) in conjunction with ocular surgery.

There is the potential for cross-sensitivity to acetylsalicylic acid, phenylacetic acid derivatives, and other nonsteroidal anti-inflammatory agents. Therefore, caution should be used when treating individuals who have previously exhibited sensitivities to these drugs.

PRECAUTIONS

General

All topical nonsteroidal anti-inflammatory drugs (NSAIDs) may slow or delay healing. Topical corticosteroids are also known to slow or delay healing. Concomitant use of topical NSAIDs and topical steroids may increase the potential for healing problems.

Use of topical NSAIDs may result in keratitis. In some susceptible patients continued use of topical NSAIDs may result in epithelial breakdown, corneal thinning, corneal infiltrates, corneal erosion, corneal ulceration, and corneal perforation. These events may be sight-threatening. Patients with evidence of corneal epithelial breakdown should immediately discontinue use of topical NSAIDs and should be closely monitored for corneal health.

Postmarketing experience with topical NSAIDs suggests that patients experiencing complicated ocular surgeries, corneal denervation, corneal epithelial defects, diabetes mellitus, ocular surface disease (e.g., dry eye syndrome), rheumatoid arthritis, or repeat ocular surgeries within a short period of time may be at increased risk for corneal adverse events, which may become sight-threatening. Topical NSAIDs should be used with caution in these patients.

Postmarketing experience with topical NSAIDs also suggests that use more than 24 hours prior to surgery or use beyond 14 days post surgery may increase patient risk for occurrence and severity of corneal adverse events.

It is recommended that diclofenac sodium ophthalmic solution, like other NSAIDs, be used with caution in patients with known bleeding tendencies or who are receiving other medications, which may prolong bleeding time. Use of the same bottle for both eyes is not recommended with topical eye drops that are used in association with surgery.

Results from clinical studies indicate that diclofenac sodium ophthalmic solution has no significant effect upon ocular pressure. However, elevations in intraocular pressure may occur following cataract surgery.

Information for Patients

Except for the use of a bandage hydrogel soft contact lens during the first 3 days following refractive surgery, diclofenac sodium ophthalmic solution should not be used by patients currently wearing soft contact lenses due to adverse events that have occurred in other circumstances.

Carcinogenesis, Mutagenesis, Impairment of Fertility

Long-term carcinogenicity studies in rats given diclofenac sodium in oral doses up to 2 mg/kg/day (approximately 500 times the human topical ophthalmic dose) revealed no significant increases in tumor incidence. A 2-year carcinogenicity study conducted in mice employing oral diclofenac sodium up to 2 mg/kg/day did not reveal any oncogenic potential. Diclofenac sodium did not show mutagenic potential in various mutagenicity studies including the Ames test. Diclofenac sodium administered to male and female rats at 4 mg/kg/day (approximately 1000 times the human topical ophthalmic dose) did not affect fertility.

Geriatric Use

No overall differences in safety or effectiveness have been observed between elderly and younger adult patients.

Teratogenic Effects

Pregnancy Category C. Reproduction studies performed in mice at oral doses up to 5,000 times (20 mg/kg/day) and in rats and rabbits at oral doses up to 2,500 times (10 mg/kg/day) the human topical dose have revealed no evidence of teratogenicity due to diclofenac sodium despite the induction of maternal toxicity and fetal toxicity. In rats, maternally toxic doses were associated with dystocia, prolonged gestation, reduced fetal weights and growth, and reduced fetal survival. Diclofenac sodium has been shown to cross the placental barrier in mice and rats. There are, however, no adequate and well-controlled studies in pregnant women. Because animal reproduction studies are not always predictive of human response, this drug should be used during pregnancy only if clearly needed.

Non-teratogenic Effects

Because of the known effects of prostaglandin biosynthesis inhibiting drugs on the fetal cardiovascular system (closure of ductus arteriosus), the use of diclofenac sodium ophthalmic solution during late pregnancy should be avoided.

Nursing Women

It is not known whether topical ophthalmic administration of diclofenac sodium ophthalmic solution could result in sufficient systemic absorption to produce detectable quantities in breast milk. Because many drugs are excreted in human milk, a decision should be made whether to discontinue nursing or to discontinue the drug, taking into account the importance of the drug to the mother.

Pediatric Use

Safety and effectiveness in pediatric patients have not been established.

ADVERSE REACTIONS

Ocular

Transient burning and stinging were reported in approximately 15% of patients across studies with the use of diclofenac sodium ophthalmic solution. In cataract surgery studies, keratitis was reported in up to 28% of patients receiving diclofenac sodium ophthalmic solution, although in many of these cases keratitis was initially noted prior to the initiation of treatment. Elevated intraocular pressure following cataract surgery was reported in approximately 15% of patients undergoing cataract surgery.

Lacrimation complaints were reported in approximately 30% of case studies undergoing incisional refractive surgery. The following adverse reactions were reported in approximately 10% or less of the patients: abnormal vision, acute elevated IOP, blurred vision, conjunctivitis, corneal deposits, corneal edema, corneal opacity, corneal lesions, discharge, eyelid swelling, eye pain, injection (redness), iritis, irritation, itching, lacrimation disorder, and ocular allergy.

Systemic

The following adverse reactions were reported in 3% or less of the patients: abdominal pain, asthenia, chills, dizziness, facial edema, fever, headache, insomnia, nausea, pain, rhinitis, viral infection, and vomiting.

Clinical Practice

The following reactions have been identified during postmarketing use of topical diclofenac sodium ophthalmic solution, 0.1% in clinical practice. Because they are reported voluntarily from a population of unknown size, estimates of frequency cannot be made. The reactions, which have been chosen for inclusion due to either their seriousness, frequency of reporting, possible causal connection to topical diclofenac sodium ophthalmic solution, 0.1%, or a combination of these factors, include corneal erosion, corneal infiltrates, corneal perforation, corneal thinning, corneal ulceration, and epithelial breakdown (see).

To report SUSPECTED ADVERSE REACTIONS, contact Bausch & Lomb Incorporated at 1-800-553-5340 or FDA at 1-800-FDA-1088 or www.fda.gov/medwatch.

OVERDOSAGE

Overdosage will not ordinarily cause acute problems. If diclofenac sodium ophthalmic solution is accidentally ingested, fluids should be taken to dilute the medication.

DOSAGE AND ADMINISTRATION

Cataract Surgery

One drop of diclofenac sodium ophthalmic solution should be applied to the affected eye, 4 times daily beginning 24 hours after cataract surgery and continuing throughout the first 2 weeks of the postoperative period.

Corneal Refractive Surgery

One or two drops of diclofenac sodium ophthalmic solution should be applied to the operative eye within the hour prior to corneal refractive surgery. Within 15 minutes after surgery, one or two drops should be applied to the operative eye and continued 4 times daily for up to 3 days.

HOW SUPPLIED

Diclofenac sodium ophthalmic solution, 0.1% (1 mg/mL) sterile solution is supplied in a low-density polyethylene (LDPE) white bottle with a LDPE Dropper Tip and a polypropylene gray cap. The 2.5 mL fill and the 5 mL fill are supplied in a 7.5 mL size bottle.
2.5 mL NDC 24208-457-25
5 mL NDC 24208-457-05

Store at 20°C to 25°C (68°F to 77°F). PROTECT FROM LIGHT.

Dispense in original, unopened container only.

Distributed by:
Bausch & Lomb Americas Inc.
Bridgewater, NJ 08807 USA
Manufactured by:
Bausch & Lomb Incorporated
Tampa, FL 33637 USA
© 2022 Bausch & Lomb Incorporated or its affiliates

Revised: June 2022

9057308 (Folded)
9057208 (Flat)

Package/Label Display Panel – 5 mL carton

NDC24208-457-05

Diclofenac
Sodium
Ophthalmic
Solution
0.1%
(Sterile)

FOR TOPICAL
APPLICATION
IN THE EYE

[Eye Image]

Rx only 5 mL

BAUSCH + LOMB

9542403
AB45707